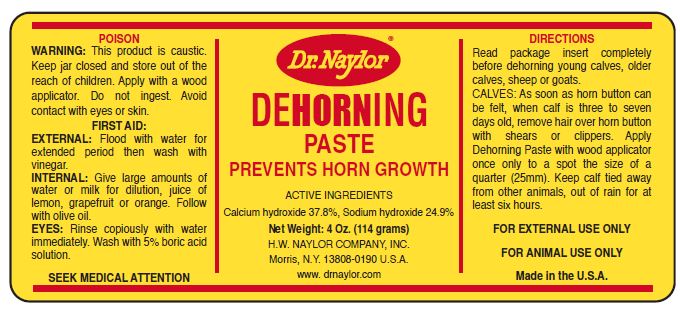 DRUG LABEL: Dehorning 
NDC: 15878-311 | Form: PASTE
Manufacturer: H. W. Naylor Company Inc.
Category: animal | Type: OTC ANIMAL DRUG LABEL
Date: 20231116

ACTIVE INGREDIENTS: Calcium Hydroxide 63 mg/1 g; Sodium Hydroxide 41 mg/1 g
INACTIVE INGREDIENTS: Ferric Oxide Red; Glycerin

DEHORNING PASTE

Active Ingredients

Calcium hydroxide 37.8%, Sodium hydroxide 24.9%

Purpose

PREVENTS HORN GROWTH

Directions

Read package insert completely before dehorning young calves, older calves, sheep or goats.

CALVES: As soon as horn button can be felt, when calf is three to seven days old, remove hair over horn button with shears or clippers. Apply Dehorning Paste with wood applicator once only to a spot the size of a quarter (25mm). Keep calf tied away from other animals, out of rain for at least six hours.

Safety

FOR EXTERNAL USE ONLY

FOR ANIMAL USE ONLY

Other Ingredients

Iron Oxide Color
Glycerin

Questions?

www.drnaylor.com

Package Insert

Directions for Using
Dr. Naylor® DeHorning Paste

Read this sheet completely before dehorning any animal.

WHEN TO DEHORN

Dr. Naylor Dehorning Paste is best used on calves up to eight (8) weeks of age. It is most easily used on very young calves. The younger the calf is when treated, the better. Shock and pain are negligible and dehorning is quickly and easily done. Dehorning Paste may be used in most areas at any time of the year; there is no cutting, no bleeding, no fly problems!

HOW TO DEHORN

ALL ANIMALS: Be careful to apply a thin, even coating of Dehorning Paste, and only as directed. Remove hair over horn button (bud) with shears or clippers in order to see that application is in the right place and in direct contact with the skin. To contain the paste, apply a ring of Dr. Naylor® Udder Balm or petroleum jelly beyond the Paste application area. If treated calves are confined in pens, tie them away from other animals to prevent rubbing paste on one another. Do not allow treated animals to nurse. Keep animals out of rain after Dehorning Paste has been applied.

YOUNG CALVES: As soon as horn button (bud) can be felt, remove hair over horn button and adjacent area with shears or clippers. On animals under one (1) week old apply a thin even film of Dehorning Paste over horn button and on a small ring of adjacent skin (horn growth epithelium) about the size of a five-cent coin (20 mm). On animals over seven days old apply Paste to a larger spot, the size of a quarter (25mm). Use a wood applicator and apply paste once only.

OLDER CALVES: To dehorn calves six to eight weeks old whose horn buttons have started to grow, remove hair and use a small scraper or file to roughen a ring of skin about 3/8 inches (10mm) wide around the base of the horn button. Do not draw blood. Apply a thin even film of Paste over the horn button and the roughened ring around the base of the horn button. Apply once only.

LAMBS, KID GOATS: Apply Dehorning Paste as soon as possible after birth if animal is in good physical condition. Minimum discomfort is experienced and application is facilitated. Application of the Paste on lambs and kids over two weeks old is generally too late to prevent future horn growth as horns are too large, especially in males. Buck kids (males) usually have palpable horn buttons (buds) at birth. Kid does (females) are a little slower in developing horns. Clip the hair over and around horn buttons. Apply a thin even film of Dehorning Paste over horn buttons and a narrow ring of skin at the base of the horn button. This ring of skin grows the horn. Too thick an application may result in deeper penetration and activity with discomfort. Dehorn dairy bucks at 3 to 4 days, dairy goes at 4 days and always before 10 days. Pygmy bucks should be dehorned at 7 days, pygmy does at 7 to 10 days. Twenty to thirty minutes after Paste application scrape off Paste and neutralize treated area by flooding with water, then vinegar. Wash water and vinegar must not come in contact with animal’s eyes. Kids and lambs may be wrapped in a blanket for a short period to prevent rubbing treated area with their hooves.

WARNING

For external veterinary use only. This product is a form of caustic. Apply only with a wood applicator and as directed. Do not ingest. Avoid eye and skin contact. Use gloves to protect hands. Keep bottle tightly capped and in a safe place.

KEEP FROM REACH OF CHILDREN

www.drnaylor.com
www.dehorning.com

H.W. Naylor Company, Inc.
Morris, NY 13808-019 U.S.A.

Save directions for future use.

Principal Display Panel

Dr. Naylor®
DEHORNING PASTE
PREVENTS HORN GROWTH
Net Weight: 4 Oz. (114 grams)
H.W. NAYLOR COMPANY, INC.
Morris, N.Y. 13808-0190 U.S.A.
www.drnaylor.com
POISON
WARNING: This product is caustic. Keep jar closed and store out of the reach of children. Apply with a wood applicator. Do not ingest. Avoid contact with eyes or skin.
FIRST AID:
EXTERNAL: Flood with water for extendced period then wash with vinegar.
INTERAL: Give large amounts of water or milk for dilution, juice of lemon, grapefruit or orange. Follow with olive oil.
EYES: Rinse copiously with water immediately. Wash with 5% boric acid solution.
SEEK MEDICAL ATTENTION